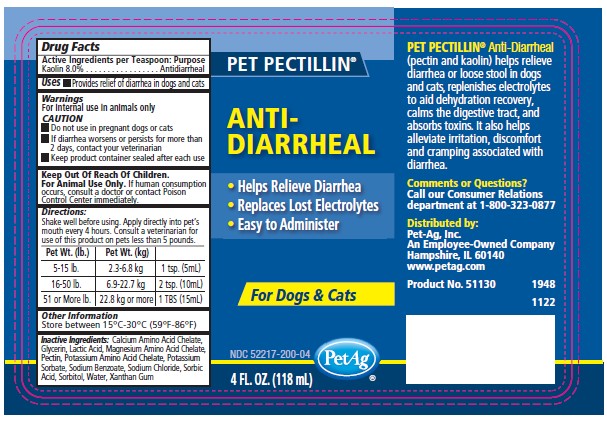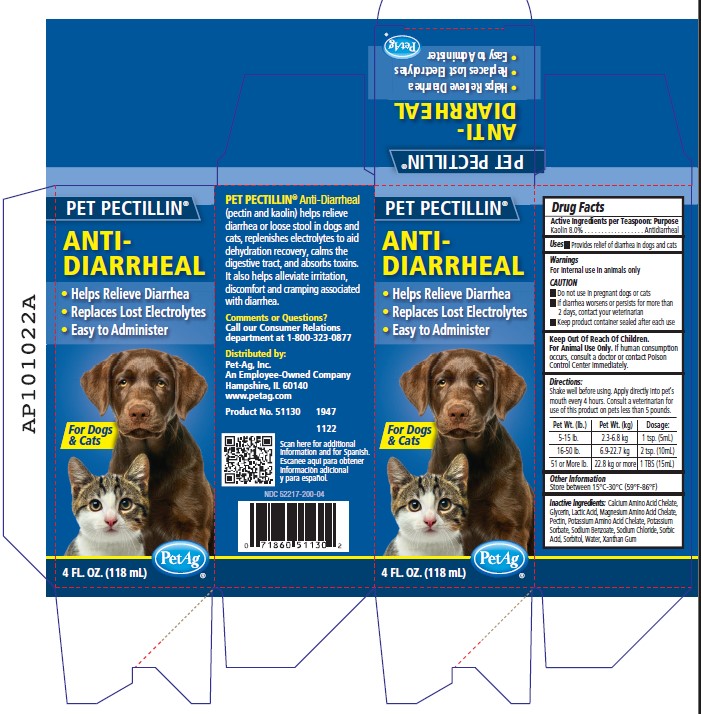 DRUG LABEL: PET Pectillin
NDC: 52217-200 | Form: SUSPENSION
Manufacturer: PBI-Gordon Corporation
Category: animal | Type: OTC ANIMAL DRUG LABEL
Date: 20241213

ACTIVE INGREDIENTS: KAOLIN 100 mg/1 mL
INACTIVE INGREDIENTS: PECTIN 8 mg/1 mL; SORBIC ACID; AMINO ACIDS

DESCRIPTION

PET Pectillin

Anti-Diarrheal

- Helps Relieve Diarrhea
- Replaces Lost Electrolytes
- Easy to Administer

For Dogs & Cats

NDC 52217-200-04

Pet-Ag

4 FL.OZ. (118 mL)

INDICATIONS AND USAGE

PET PECTILLIN Anti-Diarrheal (pectin and kaolin) helps relieve diarrhea or loose stool in dogs and cats, replenishes electrolytes to aid dehydration recovery, calms the digestive tract, and absorbs toxins. It also helps alleviate irritation, discomfort and cramping associated with diarrhea.

Comments or Questions?

Call our Consumer Relations

department at 1-800-323-0877

Distributed by:
Pet-Ag, Inc.
An Employee-Owned Company
Hampshire, IL 60140
www.petag.com

Product No. 51130

Drug Facts

Active Ingredients per Teaspoon: Purpose

Kaolin 8.0%.............Antidiarrheal

Uses

- Provides relief of diarrhea in dogs and cats

Warnings

For internal use in animals only

CAUTION

- Do not use in pregnant dogs or cats
- If diarrhea worsens or persists for more than 2 days, contact your veterinarian
- Keep product container sealed after each use

Keep out of reach of children.

For animal use only. If human consumption occurs, consult a doctor or contact Poison Control Center immediately.

Directions:

Shake well before using. Apply directly into pet's mouth every 4 hours. Consult a veterinarian for use of this product on pets less than 5 pounds.

Pet Wt. (lbs.) | Pet Wt. (kg) | Dosage:
5-15 lbs. | 2.3-6.8 kg | 1 tsp. (5mL)
16-50 lbs. | 6.9-22.7 kg | 2 tsp. (10mL)
51 or More lbs. | 22.8 kg or more | 1 TBS (15mL)

Other Information

Store between 15°C-30°C (59°F-86°F)

Inactive Ingredients

Calcium Amino Acid Chelate, Glycerin, Lactic Acid, Magnesium Amino Acid Chelate, Pectin, Potassium Amino Acid Chelate, Potassium Sorbate, Sodium Benzoate, Sodium Chloride, Sorbic Acid, Sorbitol, Water, Xantham Gum